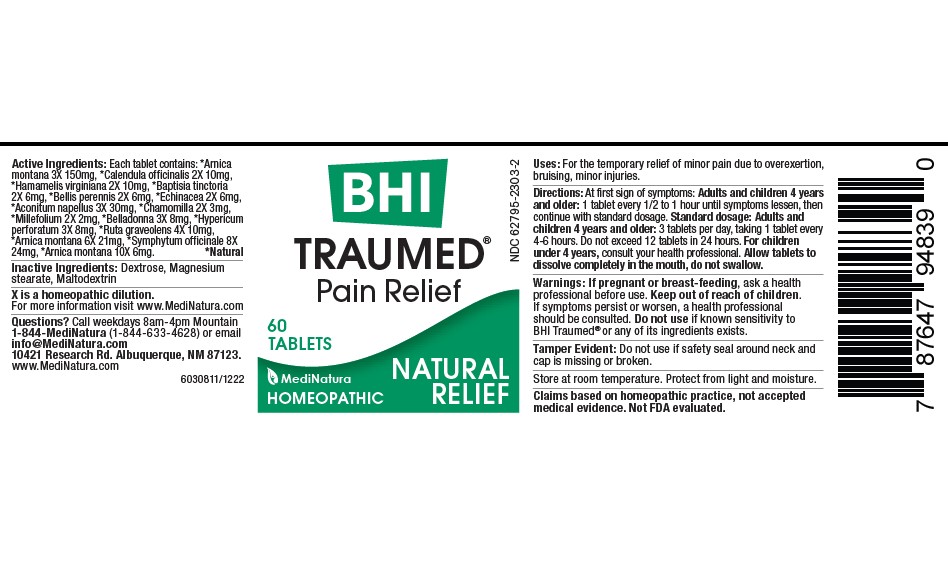 DRUG LABEL: Traumed
NDC: 62795-2303 | Form: TABLET, CHEWABLE
Manufacturer: MediNatura Inc
Category: homeopathic | Type: HUMAN OTC DRUG LABEL
Date: 20230321

ACTIVE INGREDIENTS: ARNICA MONTANA WHOLE 3 [hp_X]/1 1; CALENDULA OFFICINALIS FLOWERING TOP 2 [hp_X]/1 1; HAMAMELIS VIRGINIANA ROOT BARK/STEM BARK 2 [hp_X]/1 1; BAPTISIA TINCTORIA ROOT 2 [hp_X]/1 1; BELLIS PERENNIS WHOLE 2 [hp_X]/1 1; ECHINACEA ANGUSTIFOLIA WHOLE 2 [hp_X]/1 1; ACONITUM NAPELLUS WHOLE 3 [hp_X]/1 1; MATRICARIA CHAMOMILLA WHOLE 2 [hp_X]/1 1; ACHILLEA MILLEFOLIUM WHOLE 2 [hp_X]/1 1; ATROPA BELLADONNA 3 [hp_X]/1 1; HYPERICUM PERFORATUM WHOLE 3 [hp_X]/1 1; RUTA GRAVEOLENS FLOWERING TOP 4 [hp_X]/1 1; COMFREY ROOT 8 [hp_X]/1 1
INACTIVE INGREDIENTS: Dextrose; MAGNESIUM STEARATE; Maltodextrin

Traumed

Uses:

For the temporary relief of minor pain due to overexertion,
bruising, minor injuries.–

Warnings:

If pregnant or breast-feeding, ask a health
professional before use. Keep out of reach of children.
If symptoms persist or worsen, a health professional
should be consulted. Do not use if known sensitivity to
BHI Traumed® or any of its ingredients exists.–

Directions:

At first sign of symptoms: Adults and children 4 years
and older: 1 tablet every 1/2 to 1 hour until symptoms lessen, then
continue with standard dosage. Standard dosage: Adults and
children 4 years and older: 3 tablets per day, taking 1 tablet every
4-6 hours. Do not exceed 12 tablets in 24 hours. For children
under 4 years, consult your health professional. Allow tablets to
dissolve completely in the mouth, do not swallow

Keep out of reach of children.

Purpose

Pain Relief

Active Ingredients:

Each tablet contains: *Arnica
montana 3X 150mg, *Calendula officinalis 2X 10mg,
*Hamamelis virginiana 2X 10mg, *Baptisia tinctoria
2X 6mg, *Bellis perennis 2X 6mg, *Echinacea 2X 6mg,
*Aconitum napellus 3X 30mg, *Chamomilla 2X 3mg,
*Millefolium 2X 2mg, *Belladonna 3X 8mg, *Hypericum
perforatum 3X 8mg, *Ruta graveolens 4X 10mg,
*Arnica montana 6X 21mg, *Symphytum officinale 8X
24mg, *Arnica montana 10X 6mg. *Natural

Inactive Ingredients

Dextrose, Magnesium
stearate, Maltodextrin

PACKAGE LABEL

Add image transcription here...